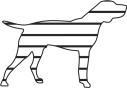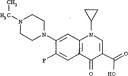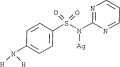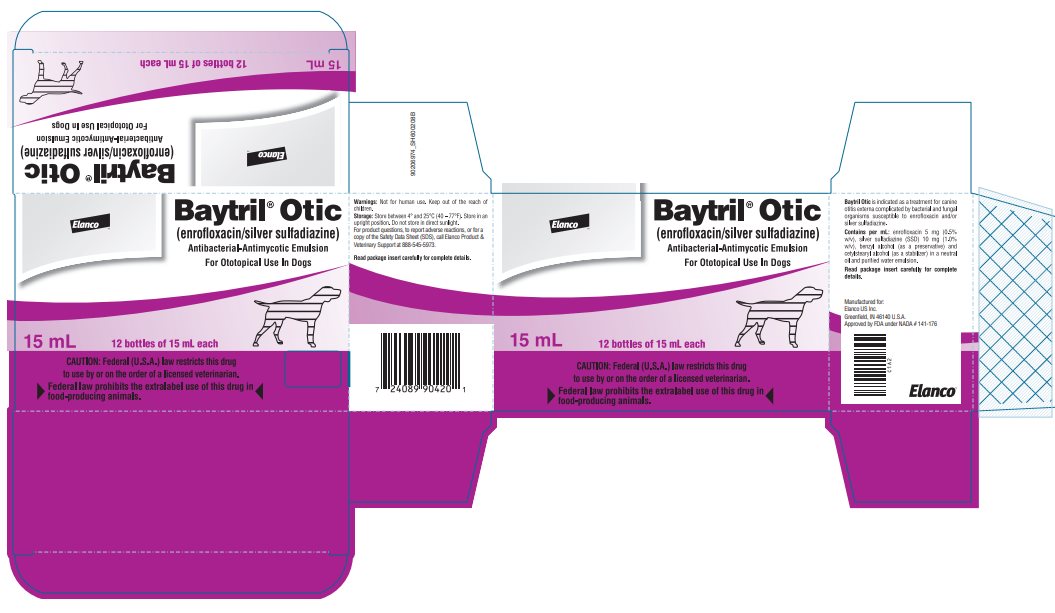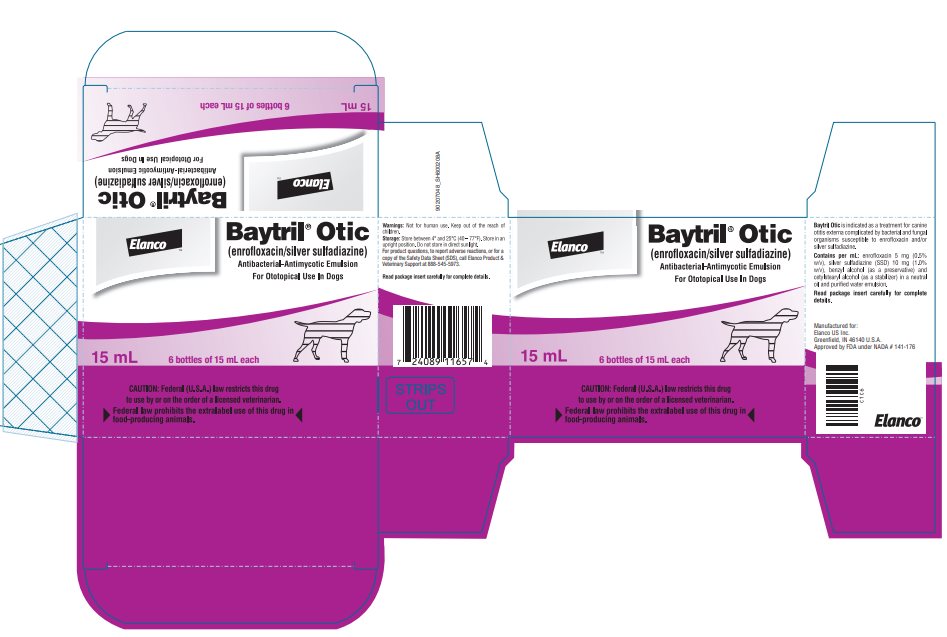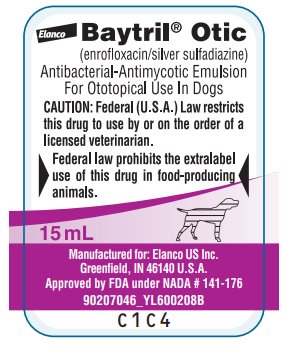 DRUG LABEL: BAYTRIL OTIC
NDC: 58198-0076 | Form: EMULSION
Manufacturer: Elanco US Inc.
Category: animal | Type: PRESCRIPTION ANIMAL DRUG LABEL
Date: 20250123

ACTIVE INGREDIENTS: ENROFLOXACIN 5 mg/1 mL; SILVER SULFADIAZINE 10 mg/1 mL

Baytril® Otic
(enrofloxacin/silver sulfadiazine)
Antibacterial-Antimycotic Emulsion

For Ototopical Use In Dogs

Caution: Federal (U.S.A.) Law restricts this drug to use by or on the order of a licensed veterinarian.

Federal law prohibits the extralabel use of this drug in food-producing animals.

PRODUCT DESCRIPTION:

Each milliliter of Baytril Otic contains: enrofloxacin 5 mg (0.5% w/v), silver sulfadiazine (SSD) 10 mg (1.0% w/v), benzyl alcohol (as a preservative) and cetylstearyl alcohol (as a stabilizer) in a neutral oil and purified water emulsion. The active ingredients are delivered via a physiological carrier (a nonirritating emulsion).

CHEMICAL NOMENCLATURE AND STRUCTURE:

Enrofloxacin

1 -Cyclopropyl-7-(4-ethyl-1-piperazinyl)-6-fluoro-1, 4-dihydro-4-oxo-3-quinolinecarboxylic acid.

Silver Sulfadiazine

Benzenesulfonamide, 4-amino-N-2-pyrimidinyl-monosilver

ACTIONS:

Enrofloxacin, a 4-fluoroquinolone compound, is bactericidal with activity against a broad spectrum of both Gram negative and Gram positive bacteria. Fluoroquinolones elicit their bactericidal activities through interactions with two intracellular enzymes, DNA gyrase (DNA topoisomerase II) and DNA topoisomerase IV, which are essential for bacterial DNA transcription, synthesis and replication. It is believed that fluoroquinolones actively bind with bacterial DNA:ENZYME complexes and thereby inhibit the essential processes catalyzed by the enzymes (DNA supercoiling and chromosomal decatenation).^1 The ultimate outcome of the fluoroquinolone intervention is DNA fragmentation and bacterial cell death.^2,3

Silver sulfadiazine (SSD) is synthesized from silver nitrate and sodium sulfadiazine.^4 This compound has a wide spectrum of antimicrobial activity against Gram negative and Gram positive bacteria and is also an effective antimycotic.^5,6 SSD suppresses microbial growth through inhibition of DNA replication and modification of the cell membrane.

MICROBIOLOGY:

In clinical field trials, Baytril Otic demonstrated elimination or reduction of clinical signs associated with otitis externa and in vitro activity against cultured organisms. Baytril Otic is effective when used as a treatment for canine otitis externa associated with one or more of the following organisms: Malassezia pachydermatis, coagulase-positive Staphylococcus spp., Pseudomonas aeruginosa, Enterobacter spp., Proteus mirabilis, Streptococci spp., Aeromonas hydrophila, Aspergillus spp., Klebsiella pneumoniae, and Candida albicans.

In vitro assays, such as disk-diffusion and agar/broth-dilution, are used to determine the susceptibilities of microbes to antimicrobial therapies. Results of agar/broth-dilution assays are reported as a Minimal Inhibitory Concentration (MIC) which represents the lowest antimicrobial concentration, expressed in μg/mL, capable of inhibiting the growth of a pathogenic microorganism. MICs are used in conjunction with pharmacokinetics to predict the in vivo efficacy of systemically administered antimicrobials. Topical administration of Baytril Otic to an exudate and debris-free canal, however, will generally result in local antimicrobial concentrations that greatly exceed serum and tissue levels resulting from systemic therapy. Therefore, when using Baytril Otic as a treatment for canine otitis externa, interpret susceptibility data cautiously.

INDICATIONS:

Baytril Otic is indicated as a treatment for canine otitis externa complicated by bacterial and fungal organisms susceptible to enrofloxacin and/or silver sulfadiazine (see Microbiology section).

EFFECTIVENESS:

Due to its combination of active ingredients, Baytril Otic provides antimicrobial therapy against bacteria and fungi (which includes yeast) commonly encountered in cases of canine otitis externa.

The effectiveness of Baytril Otic was evaluated in a controlled, double-blind, multi-site clinical trial. One hundred and sixty-nine dogs (n=169), with naturally occurring active otitis externa participated in the study. The presence of active disease was verified by aural cytology, microbial culture and otoscopy/clinical scoring. Qualified cases were randomly assigned to either Baytril Otic treatment (n=113) or to a comparable placebo-based regimen (n=56). Treatments were administered twice daily for up to 14 days. Assessment of effectiveness was based on continued resolution of clinical signs 3 to 4 days following administration of the last dose.

At study conclusion, Baytril Otic was found to be a significantly more effective treatment for canine otitis externa than the placebo regimen. Based on the scoring system used to assess treatment response, therapeutic success occurred in 67% of Baytril Otic-treated infections compared to 14% with placebo (r-value^2 0.001) after 14 days of treatment.

CONTRAINDICATIONS:

Baytril Otic is contraindicated in dogs with suspected or known hypersensitivity to quinolones and/or sulfonamides.

HUMAN WARNINGS:

Not for human use. Keep out of the reach of children. Avoid contact with eyes. In case of contact, immediately flush eyes with copious amounts of water for 15 minutes. In case of dermal contact, wash skin with soap and water. Consult a physician if irritation develops or persists following ocular or dermal exposures. Individuals with a history of hypersensitivity to quinolone compounds or antibacterials should avoid handling this product. In humans, there is a risk of user photosensitization within a few hours after excessive exposure to quinolones. If excessive accidental exposure occurs, avoid direct sunlight.

PRECAUTIONS:

The use of Baytril Otic in dogs with perforated tympanic membranes has not been evaluated. Therefore, the integrity of the tympanic membrane should be evaluated before administering this product. If hearing or vestibular dysfunction is noted during the course of treatment, discontinue use of Baytril Otic.

Quinolone-class drugs should be used with caution in animals with known or suspected Central Nervous System (CNS) disorders. In such animals, quinolones have, in rare instances, been associated with CNS stimulation which may lead to convulsive seizures.

Quinolone-class drugs have been associated with cartilage erosions in weightbearing joints and other forms of arthropathy in immature animals of various species.

The safe use of Baytril Otic in dogs used for breeding purposes, during pregnancy, or in lactating bitches, has not been evaluated.

ADVERSE REACTIONS:

During clinical trials, 2 of 113 (1.7%) dogs exhibited reactions that may have resulted from treatment with Baytril Otic. Both cases displayed local hypersensitivity responses of the aural epithelium to some component within the Baytril Otic formulation. The reactions were characterized by acute inflammation of the ear canal and pinna.

For product questions, to report adverse reactions, or for a copy of the Safety Data Sheet (SDS), call Elanco Product & Veterinary Support at 888-545-5973.

For additional information about reporting adverse drug experiences for animal drugs, contact FDA at 1-888-FDA-VETS or http://www.fda.gov/reportanimalae.

SAFETY:

General Safety Study:

In a target animal safety study, Baytril Otic was administered in both ears of 24 clinically normal beagle dogs at either recommended or exaggerated dosages: 10, 30 or 50 drops applied twice daily for 42 consecutive days. A control group of 8 beagle dogs was treated by administering 50 drops of vehicle in one ear twice daily for 42 consecutive days, with the contralateral ear untreated. Erythema was noted in all groups, including both treated and untreated ears in the controls, which resolved following termination of treatment.

Oral Safety Study:

In order to test safety in case of ingestion, Baytril Otic was administered, twice daily for 14 consecutive days, to the dorsum of the tongue and to the left buccal mucosa of 6 clinically normal dogs. No adverse local or systemic reactions were reported.

DOSAGE AND ADMINISTRATION:

Shake well before each use.

Tilt head so that the affected ear is presented in an upward orientation. Administer a sufficient quantity of Baytril Otic to coat the aural lesions and the external auditory canal. As a general guide, administer 5-10 drops per treatment in dogs weighing 35 lbs. or less and 10-15 drops per treatment in dogs weighing more than 35 lbs. Following treatment, gently massage the ear so as to ensure complete and uniform distribution of the medication throughout the external ear canal. Apply twice daily for a duration of up to 14 days.

STORAGE:

Store between 4° and 25°C (40 - 77°F). Store in an upright position. Do not store in direct sunlight.

HOW SUPPLIED:

Baytril Otic (enrofloxacin/silver sulfadiazine)

Size | Presentation
15 mL | Oval plastic bottle with dropper tip and extended tip closure

REFERENCES:

1. Hooper DC and Wolfson JS. Mechanisms of quinolone action and bacterial killing in quinolone antimicrobial agents. Washington DC, American Society for Microbiology, 2nd ed., 1993: 53-75.
2. Gootz TD and Brightly KE. Fluoroquinolone antibacterial: mechanism of action, resistance and clinical aspects. Medicinal Research Reviews 1996:16 (5): 433-486.
3. Drlica K and Zhoa X. DNA gyrase, topoisomerase IV and the 4-quinolones. Microbiology and Molecular Biology Reviews 1997: 61(3): 377-392.
4. Fox CL. Silver sulfadiazine: a new topical therapy for Pseudomonas in burns. Archives of Surgery 1968: 96:184-188.
5. Wlodkowski TJ and Rosenkranz HS. Antifungal activity of silver sulfadiazine. Lancet 1973: 2:739-740.
6. Schmidt A. In vitro activity of climbazole, clotrimazole and silver sulfadiazine against isolates of Malassezia pachy-dermatis. J of Vet Medicine Series B 1997: 44:193-197.

Baytril is sold by Elanco or its affiliates and is not a product of Bayer. The product name Baytril is owned by Bayer and used under license.
Elanco and the diagonal bar logo are trademarks of Elanco or its affiliates.

Manufactured for: Elanco US Inc.
Greenfield, IN 46140 U.S.A.

© 2022 Elanco or its affiliates.

Approved by FDA under NADA # 141-176

Revised: January 2022

90207047_PA600208X

Elanco™

Principal Display Panel - 15 mL Carton Label

Baytril® Otic

(enrofloxacin/silver sulfadiazine)

Antibacterial-Antimycotic Emulsion

For Ototopical Use In Dogs

15 mL

12 bottles of 15 mL each

CAUTION: Federal (U.S.A.) law restricts this drug
to use by or on the order of a licensed veterinarian.

Federal law prohibits the extralabel use of this drug in
food-producing animals.

Baytril® Otic

(enrofloxacin/silver sulfadiazine)

Antibacterial-Antimycotic Emulsion

For Ototopical Use In Dogs

15 mL

6 bottles of 15 mL each

CAUTION: Federal (U.S.A.) law restricts this drug
to use by or on the order of a licensed veterinarian.

Federal law prohibits the extralabel use of this drug in
food-producing animals.

Principal Display Panel - 15 mL Bottle Label

Baytril® Otic

(enrofloxacin/silver sulfadiazine)

Antibacterial-Antimycotic Emulsion

For Ototopical Use In Dogs

CAUTION: Federal (U.S.A.) Law restricts
this drug to use by or on the order of a
licensed veterinarian.

Federal law prohibits the extralabel
use of this drug in food-producing
animals.

15 mL

Manufactured for: Elanco US Inc.
Greenfield, IN 46140 U.S.A.

Approved by FDA under NADA # 141-176

90207046_YL600208B

C1C4